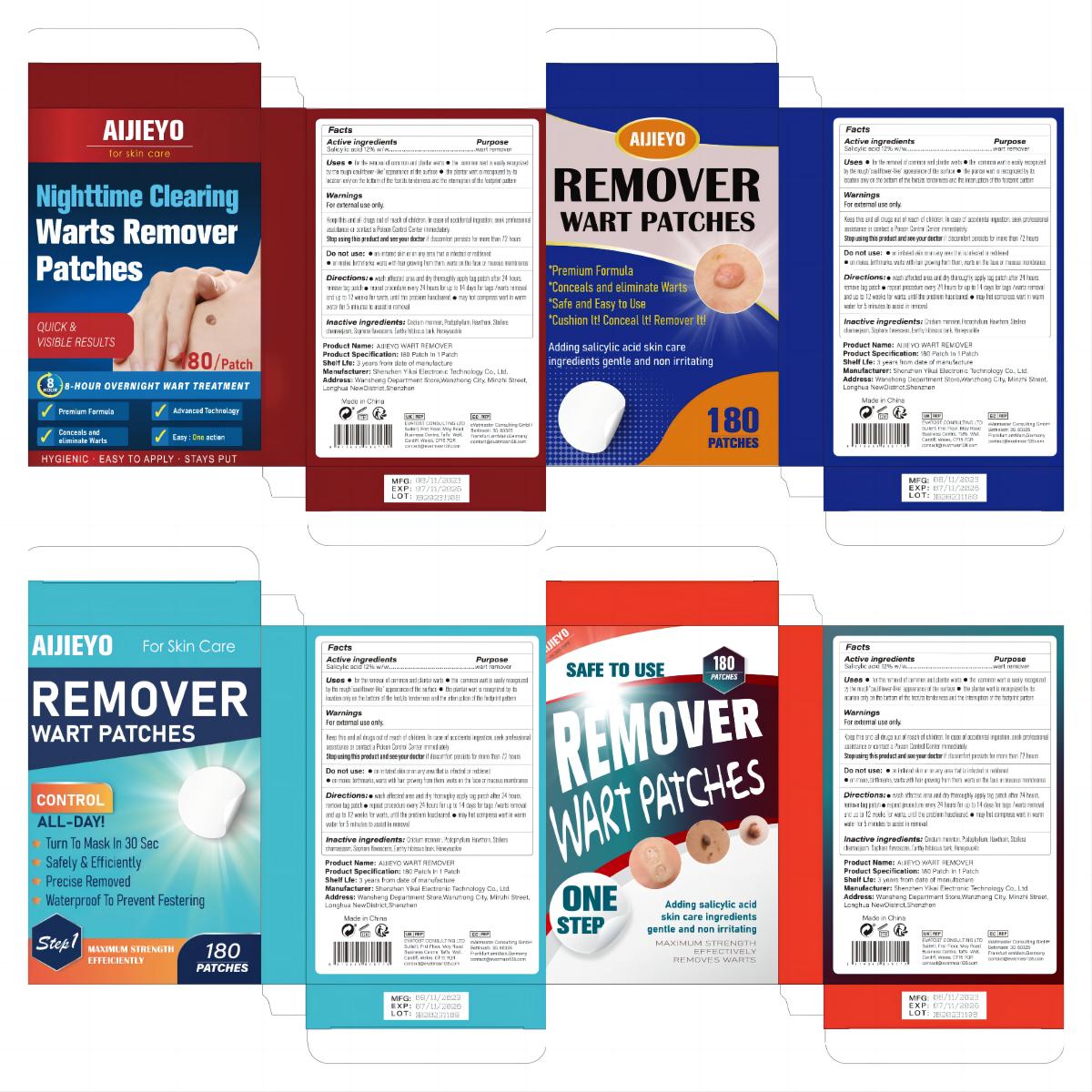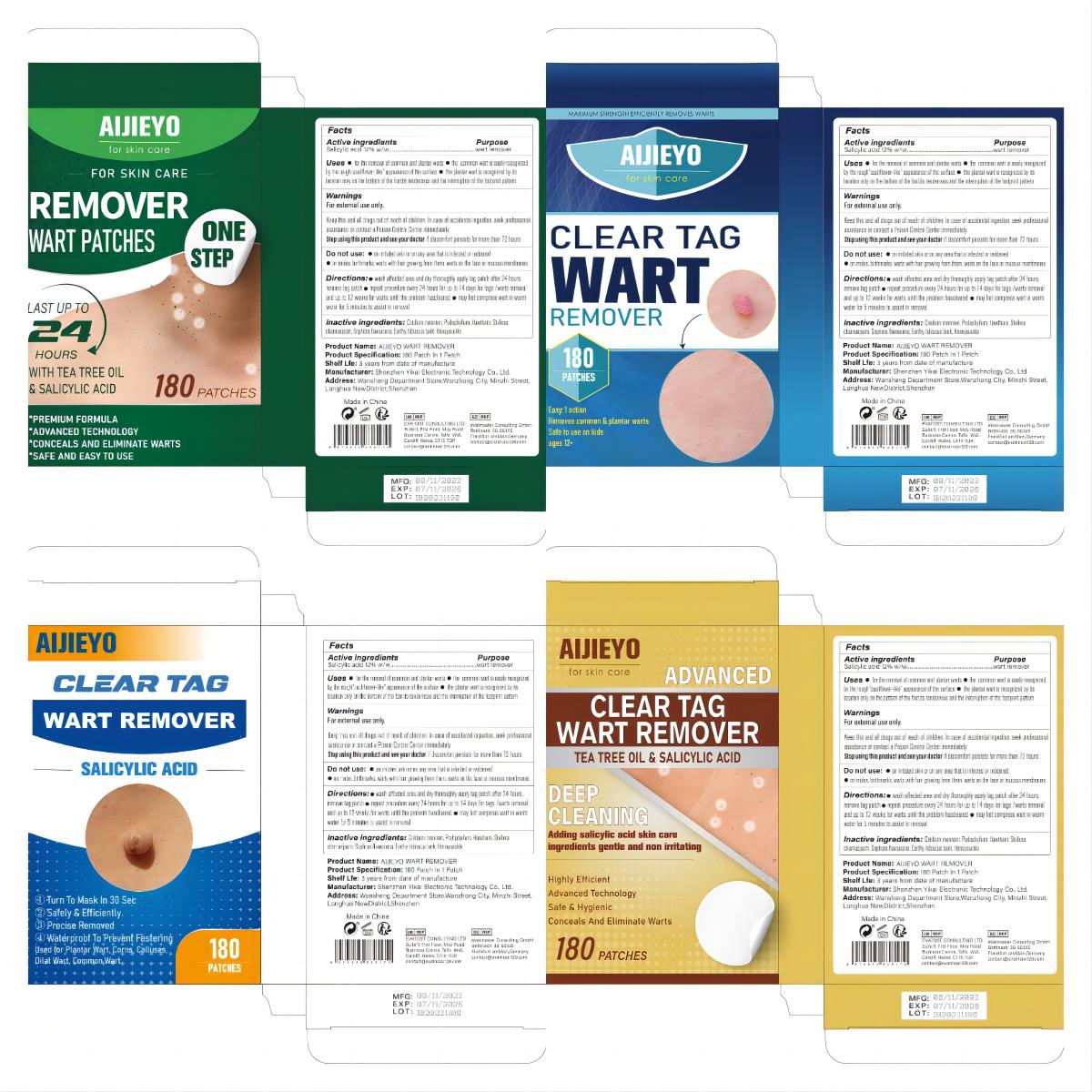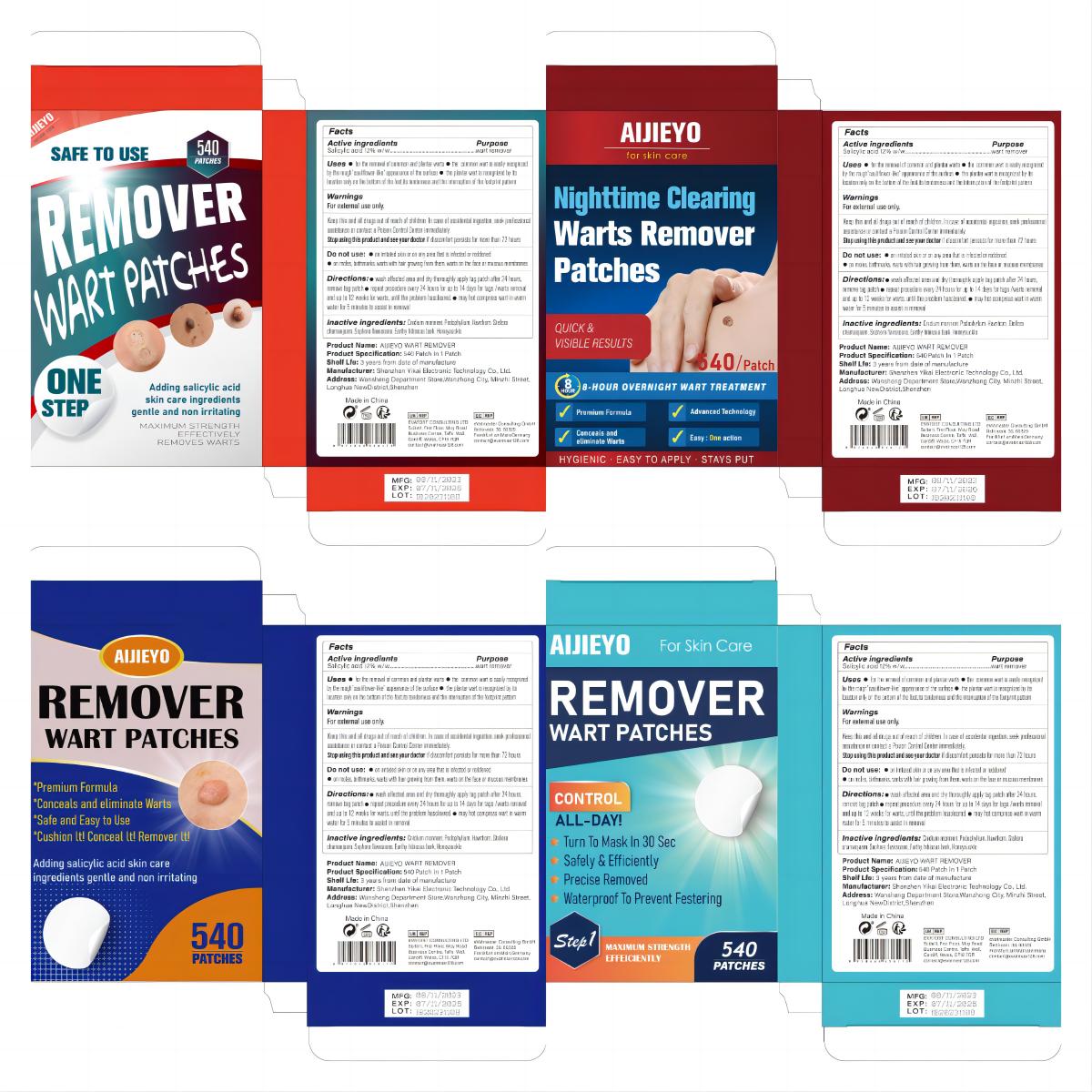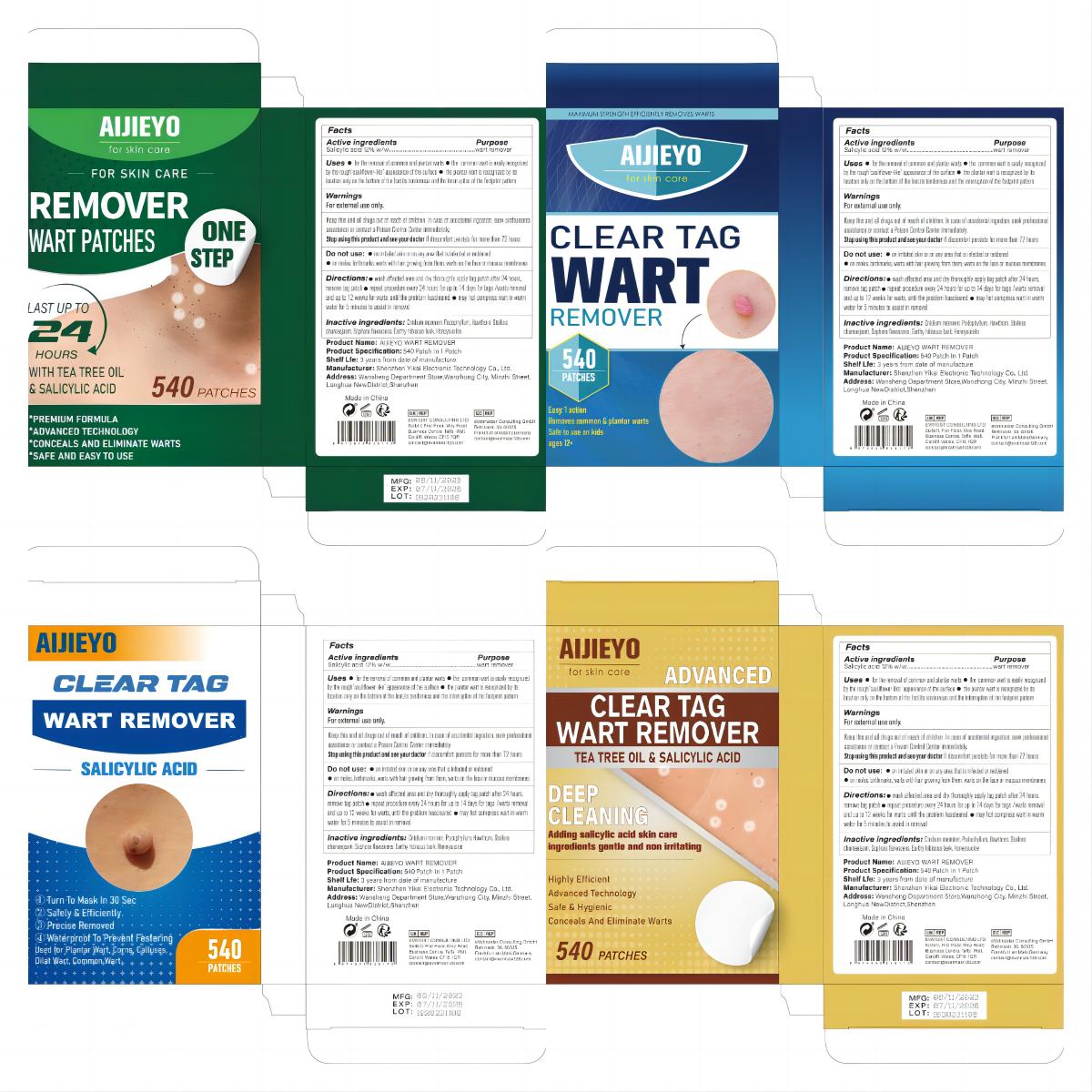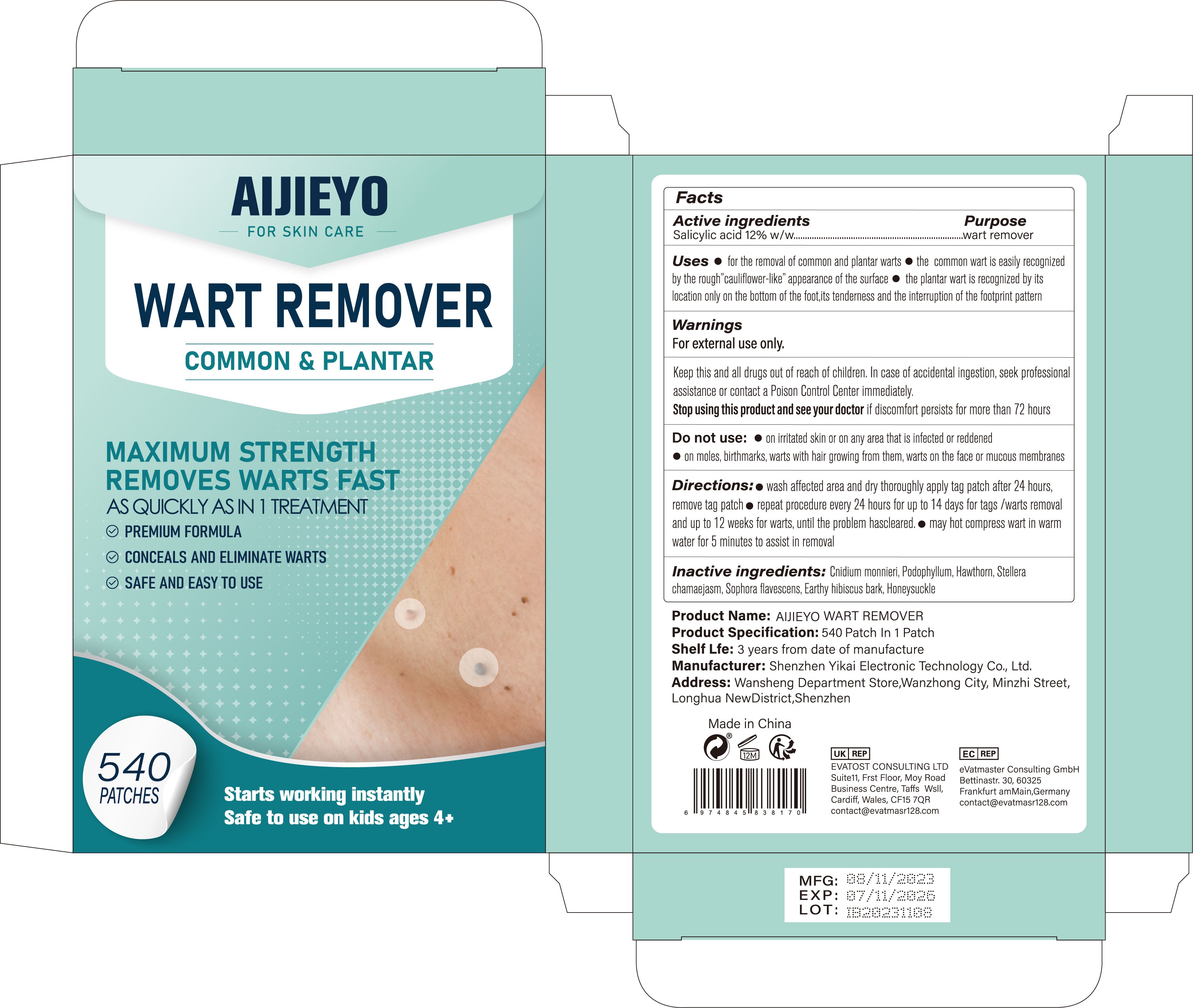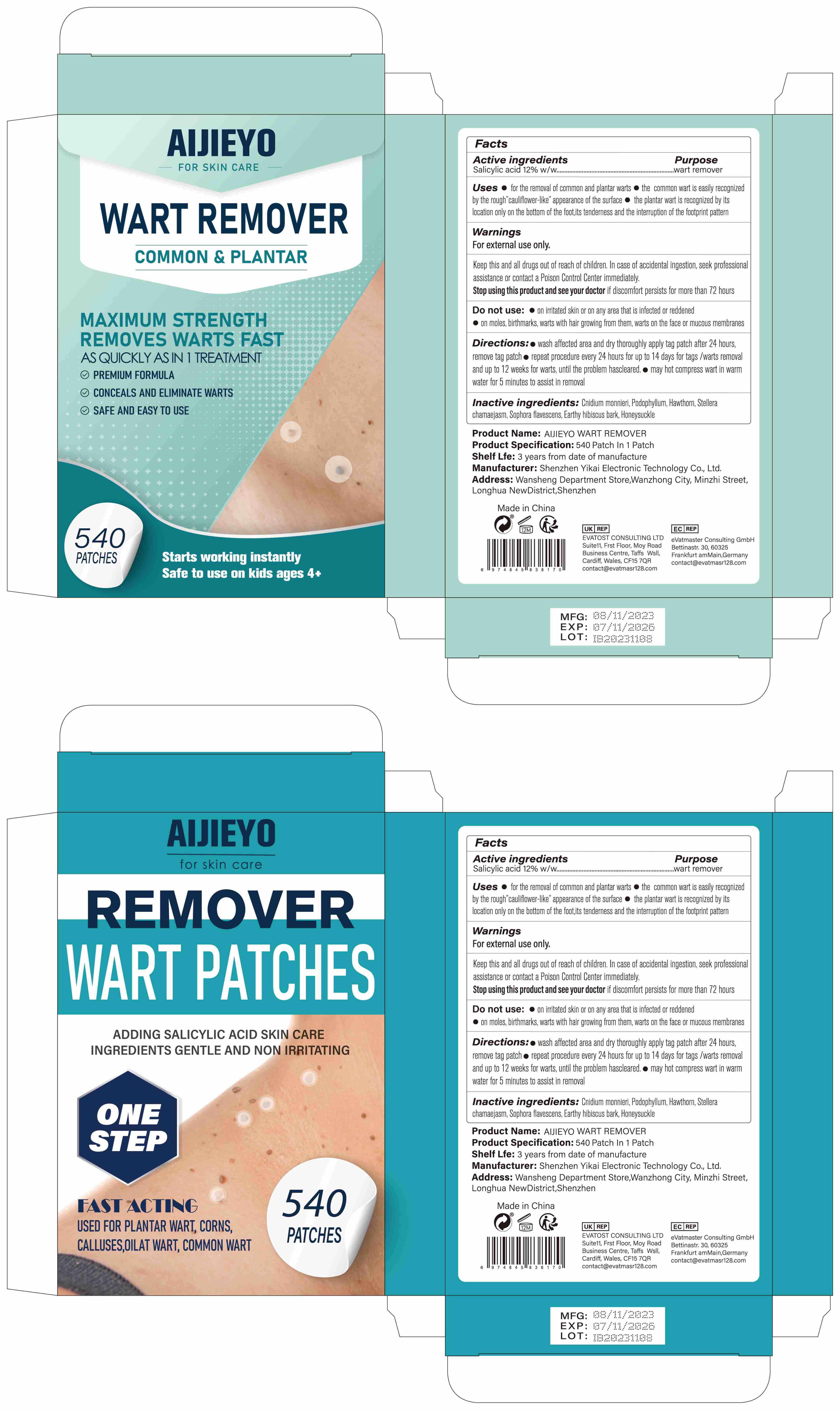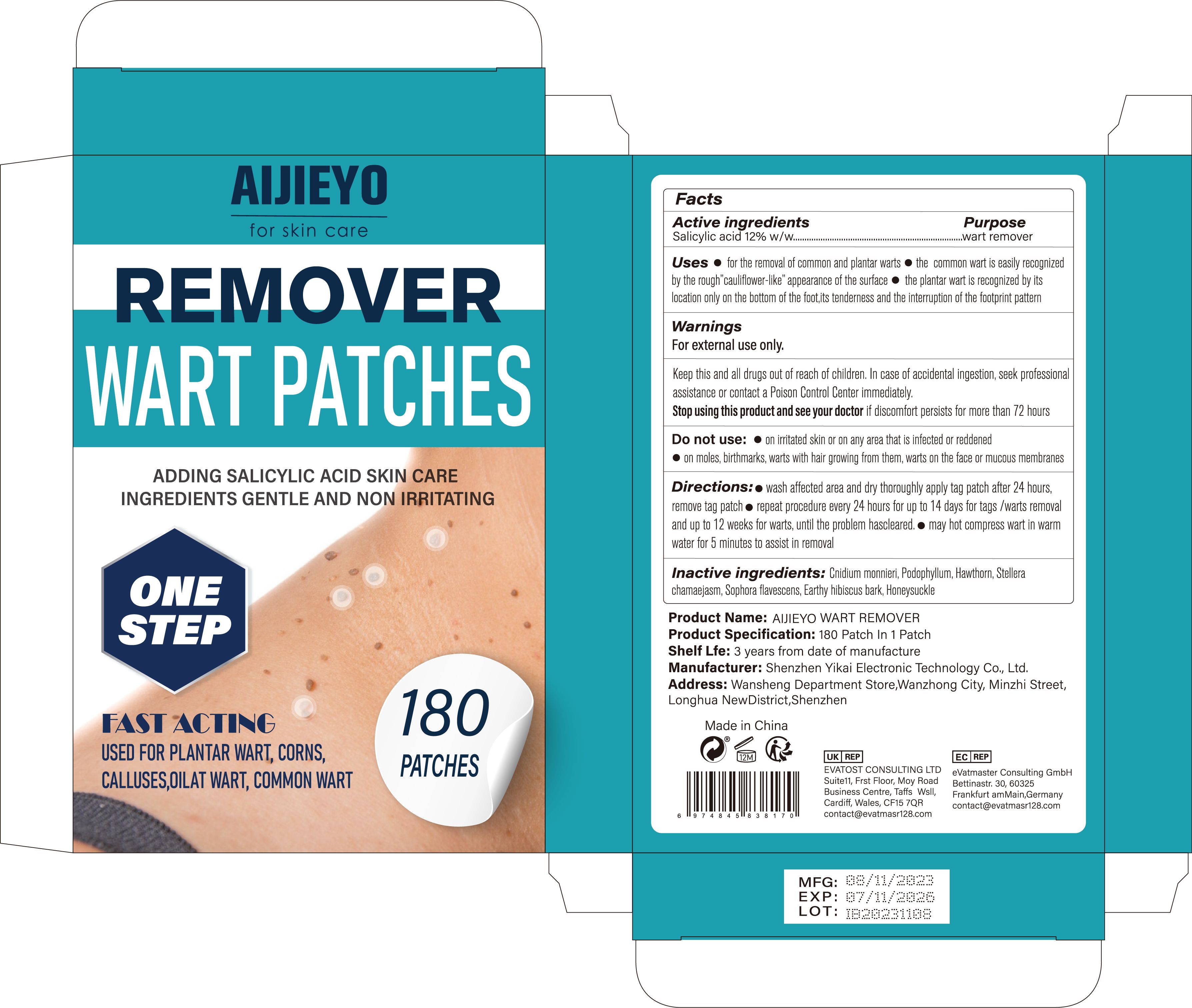 DRUG LABEL: AlJIEYO WART REMOVER
NDC: 83809-003 | Form: PATCH
Manufacturer: Shenzhen Yikai Electronic Technology Co., Ltd.
Category: otc | Type: HUMAN OTC DRUG LABEL
Date: 20250107

ACTIVE INGREDIENTS: SALICYLIC ACID 12 g/100 1
INACTIVE INGREDIENTS: PODOPHYLLUM; HAWTHORN LEAF WITH FLOWER; STELLERA CHAMAEJASME WHOLE; HIBISCUS SYRIACUS BARK; LONICERA HYPOGLAUCA FLOWER; CNIDIUM MONNIERI FRUIT OIL; SOPHORA FLAVESCENS ROOT

83809-003 Update

Active Ingredient

Salicylic acid 12%

Purpose

wart remover

Use

● for the removal of common and plantar warts

● the common wart is easily recognized by the roughcauliflower-like appearance of the surface

● the plantar wart is recognized by its location only on the bottom of the foot,its tenderness and the interruption of the footprint pattern

Warnings

For external use only.
Keep this and all drugs out of reach of children. In case of accidental ingestion, seek professional assistance or contact a Poison Control Center immediately.
Stop using this product and see your doctor if discomfort persists for more than 72 hours

Do not use

●on irritated skin or on any area that is infected or reddened

●on moles, birthmarks, warts with hair growing from them, warts on the face or mucous membranes

Keep Oot Of Reach Of Children

Please store this product out of the reach of childre

Directions

● wash affected area and dry thoroughly apply tag patch after 24 hours. remove tag patch

● repeat procedure every 24 hours for up to 14 days for tags /warts removal and up to 12 weeks for warts, until the problem hascleared.

● may hot compress wart in warm water for 5 minutes to assist in removal

Inactive ingredients

Cnidium monnieri, Podophyllum,Hawthorn, Stellera chamaejasm, Sophora flavescens, Earthy hibiscus bark, Honeysuckle